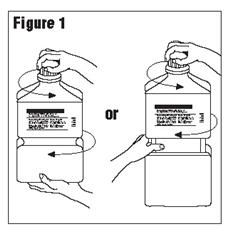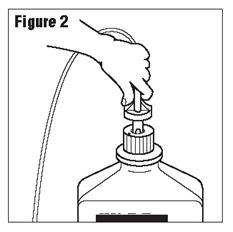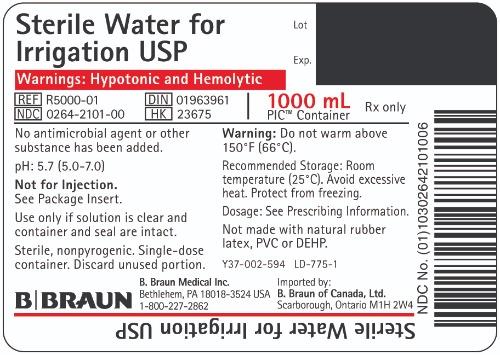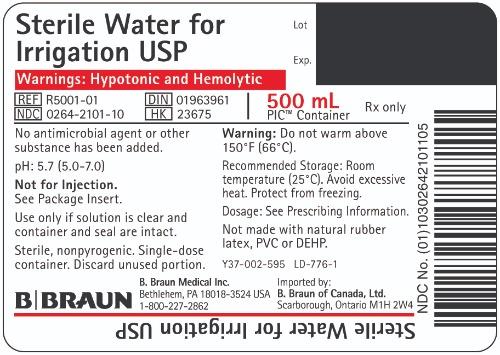 DRUG LABEL: Sterile Water
NDC: 0264-2101 | Form: IRRIGANT
Manufacturer: B. Braun Medical Inc.
Category: prescription | Type: HUMAN PRESCRIPTION DRUG LABEL
Date: 20230906

ACTIVE INGREDIENTS: WATER 1 mL/1 mL

Package Insert
PIC™ (Plastic Irrigation Containers)
Sterile Water for Irrigation USP
Rx only

DESCRIPTION

Sterile Water for Irrigation USP is a sterile, hypotonic, nonpyrogenic irrigating fluid or pharmaceutic aid (solvent) entirely composed of Sterile Water for Injection USP. It is prepared by distillation and contains no antimicrobial or bacteriostatic agents or added buffers. The pH is 5.7 (5.0–7.0)

The plastic container is a copolymer of ethylene and propylene formulated and developed for parenteral drugs. The copolymer contains no plasticizers and exhibits virtually no leachability. The plastic container is also virtually impermeable to vapor transmission and therefore, requires no overwrap to maintain the proper drug concentration. The safety of the plastic container has been confirmed by biological evaluation procedures. The material passes Class Vl testing as specified in the U.S. Pharmacopeia for Biological Tests — Plastic Containers. These tests have shown that the container is nontoxic and biologically inert.

Not made with natural rubber Latex, PVC or DEHP.

CLINICAL PHARMACOLOGY

Sterile Water for Irrigation USP is utilized for a variety of clinical indications. Because of its low refractive index (1.3325), water provides excellent visibility during endoscopic urological procedures. It is also utilized as a pharmaceutic aid, as well as in the preparation of enteral nutrient products.

Water is hypotonic and will cause hemolysis and will be readily absorbed by the tissues during surgical procedures; therefore, its use under such conditions is not recommended.

INDICATIONS AND USAGE

Sterile Water for Irrigation USP is indicated for use as an irrigating fluid or pharmaceutic aid. Sterile Water may also be used as an adjunct in the preparation of non-intravenously administered nutrient mixtures (see DOSAGE AND ADMINISTRATION).

CONTRAINDICATIONS

Not for injection.

WARNINGS

Sterile Water for Irrigation USP is hypotonic and will cause hemolysis, and is not recommended for use during surgical procedures.

After opening container, its contents should be used promptly to minimize the possibility of bacterial growth or pyrogen formation.

Discard unused portion of irrigating solution since it contains no preservative.

PRECAUTIONS

Use only if solution is clear and container and seal are intact.

ADVERSE REACTIONS

None known.

OVERDOSAGE

None known.

DOSAGE AND ADMINISTRATION

Irrigation

Use as directed by physician.

This drug product should be inspected visually for particulate matter and discoloration prior to administration, whenever solution and container permit.

Nutrient Mixtures

Sterile Water for Irrigation USP may be used to prepare non-intravenously administered nutrient mixtures. It contains no electrolytes or other added substances. Refer to preparation instructions of particular mixture to be used. The plastic container may be used for administration of non-intravenous nutrient mixture to the patient as appropriate.

HOW SUPPLIED

Sterile Water for Irrigation USP is supplied sterile and nonpyrogenic in plastic irrigating containers. The 1000 mL and 500 mL containers are packaged 16 per case.

NDC | Cat. No. | Size
Sterile Water for Irrigation USP (Canada DIN 01963961)
0264-2101-00 | R5000-01 | 1000 mL
0264-2101-10 | R5001-01 | 500 mL

Exposure of pharmaceutical products to heat should be minimized. Avoid excessive heat. Protect from freezing. It is recommended that the product be stored at room temperature (25°C); however, brief exposure up to 40°C does not adversely affect the product.

Do not warm above 150°F (66°C).

Revised: May 2023

PIC is a trademark of B. Braun Medical Inc.

Directions for Use of PIC™ (Plastic Irrigation Container)

Not for injection.

Aseptic technique is required.

1. Caution – Before use, perform the following checks:
  (a) Read the label. Ensure solution is the one ordered and is within the expiration date.
  (b) Invert container and inspect the solution in good light for cloudiness, haze, or particulate matter; check the container for leakage or damage. Any container which is suspect should not be used.
  Use only if solution is clear and container and seal are intact.
  Single-dose container. Discard unused portion.
2. Outer Closure Removal – Grasp the container with one hand and turn the breakaway ring counterclockwise with the other hand until slight resistance is felt. Then, twisting the container in the opposite direction, turn the breakaway ring sharply until the entire outer cap is loose and can be lifted off. (Figure 1)
3. Connect the administration set through the sterile set port according to set instructions (Figure 2) or remove screw cap and pour.
4. Do not warm above 150°F (66°C) to assure minimal bottle distortion. Keep bottles upright.

B. Braun Medical Inc.
Bethlehem, PA 18018-3524 USA
1-800-227-2862

Imported by:
B. Braun of Canada, Ltd.
Scarborough, Ontario M1H 2W4

Y36-003-075 LD-774-1

PRINCIPAL DISPLAY PANEL - 1000 mL Container

Sterile Water for Irrigation USP

Warnings: Hypotonic and Hemolytic

REF R5000-01
NDC 0264-2101-00
DIN 01963961
HK 23675

1000 mL
PIC™ Container

Rx only

Lot
Exp.

No antimicrobial agent or other substance has been added.

pH: 5.7 (5.0-7.0)

Not for Injection.
See Package Insert.

Use only if solution is clear and container and seal are intact.

Sterile, nonpyrogenic. Single-dose container. Discard unused portion.

Warning: Do not warm above 150°F (66°C).

Recommended Storage: Room temperature (25°C). Avoid excessive heat. Protect from freezing.

Dosage: See Prescribing Information.

Not made with natural rubber latex, PVC or DEHP.

Y37-002-594 LD-775-1

B. Braun Medical Inc.
Bethlehem, PA 18018-3524 USA
1-800-227-2862

Imported by:
B. Braun of Canada, Ltd.
Scarborough, Ontario M1H 2W4

Sterile Water for Irrigation USP

PRINCIPAL DISPLAY PANEL - 500 mL Container

Sterile Water for Irrigation USP

Warnings: Hypotonic and Hemolytic

REF R5001-01
NDC 0264-2101-10
DIN 01963961
HK 23675

500 mL
PIC™ Container

Rx only

Lot
Exp.

No antimicrobial agent or other substance has been added.

pH: 5.7 (5.0-7.0)

Not for Injection.
See Package Insert.

Use only if solution is clear and container and seal are intact.

Sterile, nonpyrogenic. Single-dose container. Discard unused portion.

Warning: Do not warm above 150°F (66°C).

Recommended Storage: Room temperature (25°C). Avoid excessive heat. Protect from freezing.

Dosage: See Prescribing Information.

Not made with natural rubber latex, PVC or DEHP.

Y37-002-595 LD-776-1

B. Braun Medical Inc.
Bethlehem, PA 18018-3524 USA
1-800-227-2862

Imported by:
B. Braun of Canada, Ltd.
Scarborough, Ontario M1H 2W4

Sterile Water for Irrigation USP